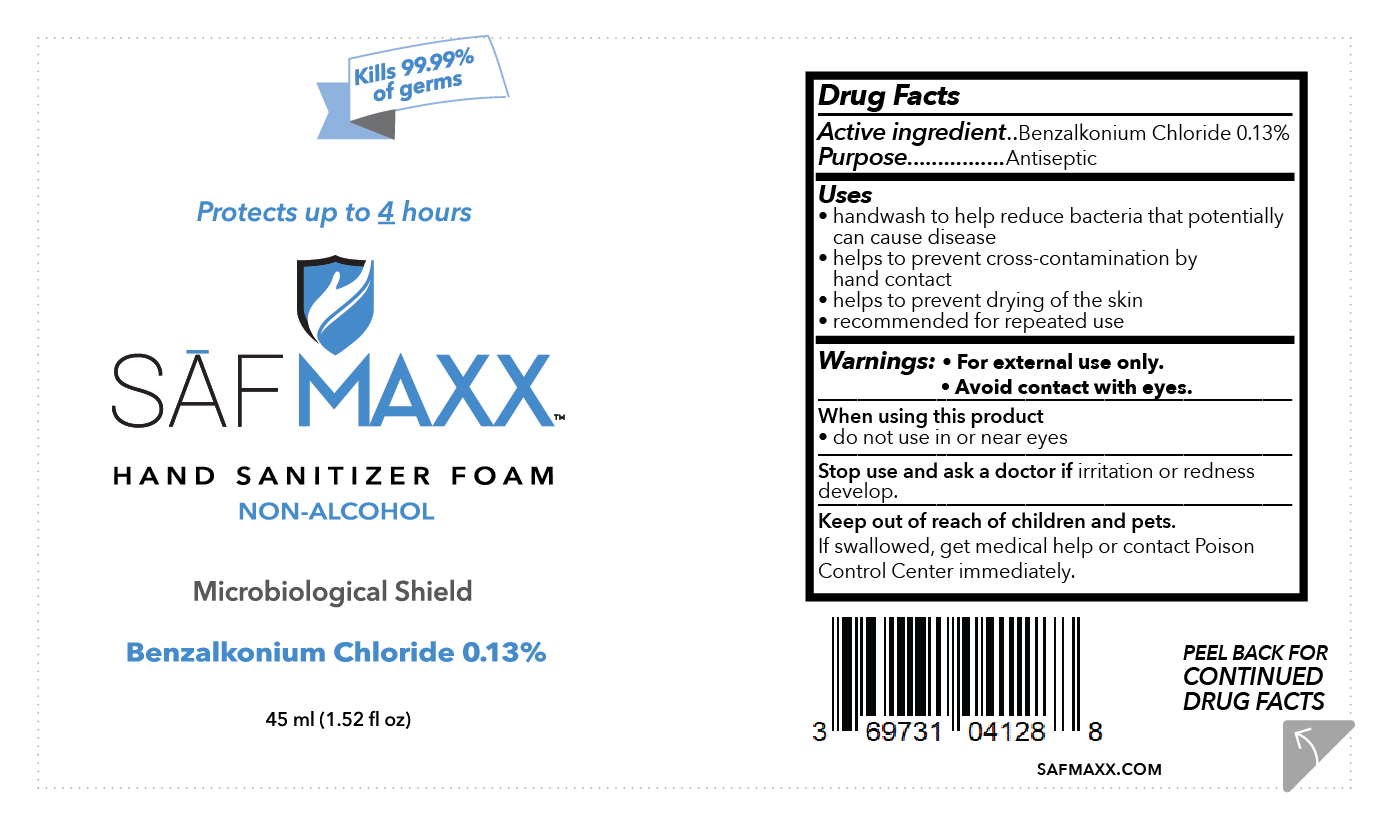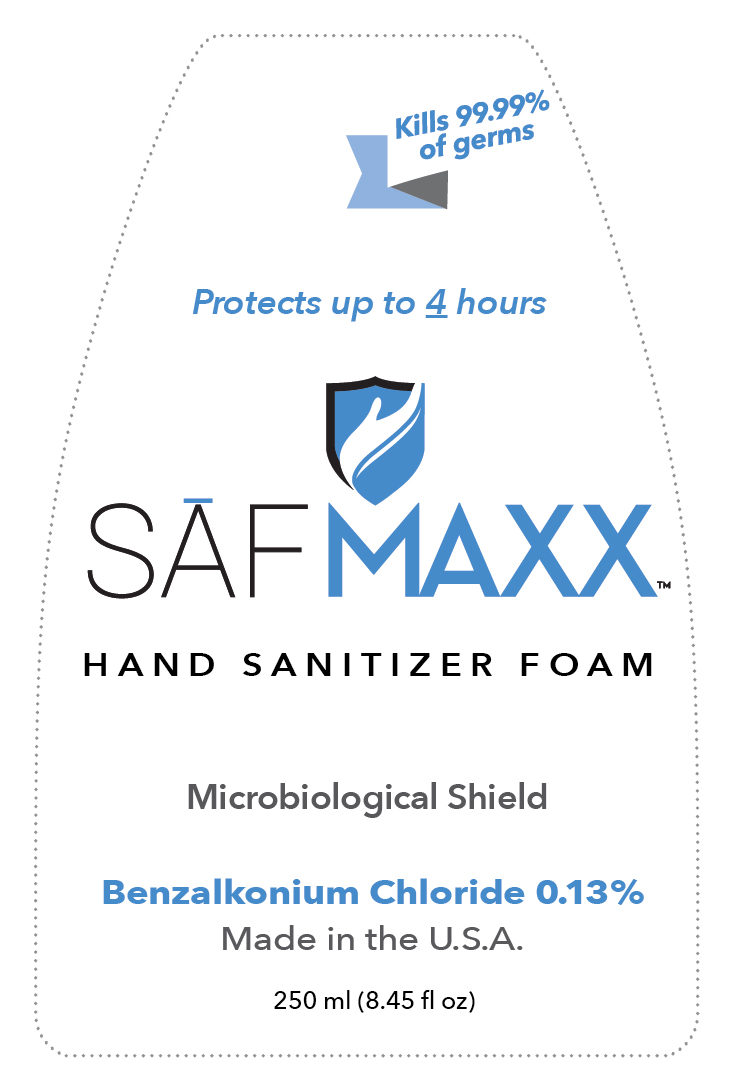 DRUG LABEL: SAFMAXX Hand Sanitizer
NDC: 69731-041 | Form: LIQUID
Manufacturer: G&N Enterprise,LLC
Category: otc | Type: HUMAN OTC DRUG LABEL
Date: 20201117

ACTIVE INGREDIENTS: BENZALKONIUM CHLORIDE 1.3 mg/1 mL
INACTIVE INGREDIENTS: WATER; COCAMIDOPROPYL BETAINE; GLYCERIN; POLOXAMER 124; BENZYL ALCOHOL; PHENOXYETHANOL; FD&C BLUE NO. 1

SAFMAXX Hand Sanitizer

Active ingredient

Benzalkonium Chloride 0.13%

Purpose

Antiseptic

Uses

- handwash to help reduce bacteria that potentially can cause disease

- helps to prevent cross-contamination by hand contact

- helps to prevent drying of the skin

- recommended for repeated use

Warnings

For external use only

When using this product do not use in or near eyes

Stop use and ask a doctor if irritation or redness develop.

Keep out of reach of children.

If swallowed, seek medical attention or contact a Poison Control Center immediately.

Directions

- apply appropriate amount of product into palm of hand

- rub thouroughtly over all surfaces of both hands for at least 20 seconds
- rub hands together until dry

Other information

store in a cool, dry place below 104o F (40o C)

Inactive ingredients

Water, cocamidopropyl betaine, glycerine, polozamer 124, benzyl alcohol, phenoxyethanol,FD&C Blue No.1

Questions?

Contact G&N Enterprise, LLC at 800-290-6816 Mon-Fri 9 am-5 pm CST

PACKAGE LABEL

SAFMAXX

Hand Sanitizer

Non_Alcohol

Microbiological Shield

Made in the USA

Benzalkonium Chloride 0.13%